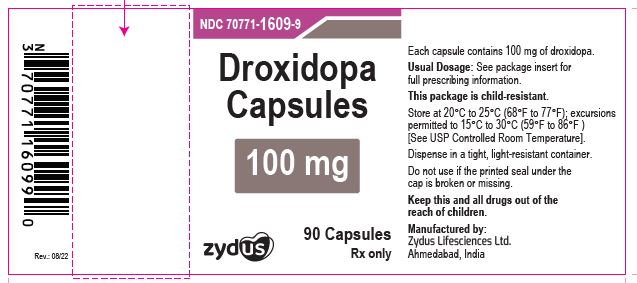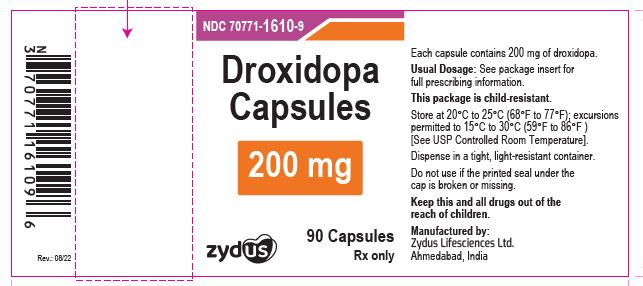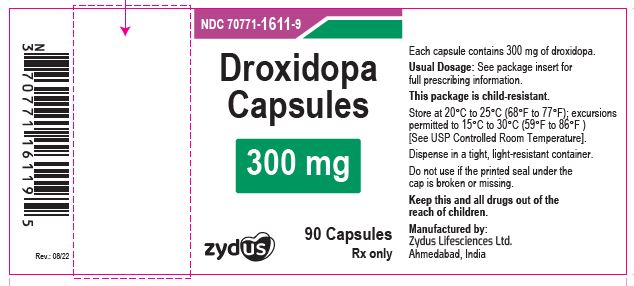 DRUG LABEL: Droxidopa
NDC: 70771-1609 | Form: CAPSULE
Manufacturer: Zydus Lifesciences Limited
Category: prescription | Type: HUMAN PRESCRIPTION DRUG LABEL
Date: 20241128

ACTIVE INGREDIENTS: DROXIDOPA 100 mg/1 1
INACTIVE INGREDIENTS: FD&C BLUE NO. 1; FD&C RED NO. 40; FERROSOFERRIC OXIDE; GELATIN; MAGNESIUM STEARATE; MANNITOL; POTASSIUM HYDROXIDE; PROPYLENE GLYCOL; SHELLAC; SODIUM LAURYL SULFATE; STARCH, CORN; TITANIUM DIOXIDE; WATER

Droxidopa Capsules

PACKAGE LABEL.PRINCIPAL DISPLAY PANEL

NDC 70771-1609-9

Droxidopa Capsules, 100 mg

90 Capsules

Rx only

NDC 70771-1610-9

Droxidopa Capsules, 200 mg

90 Capsules

Rx only

NDC 70771-1611-9

Droxidopa Capsules, 300 mg

90 Capsules

Rx only